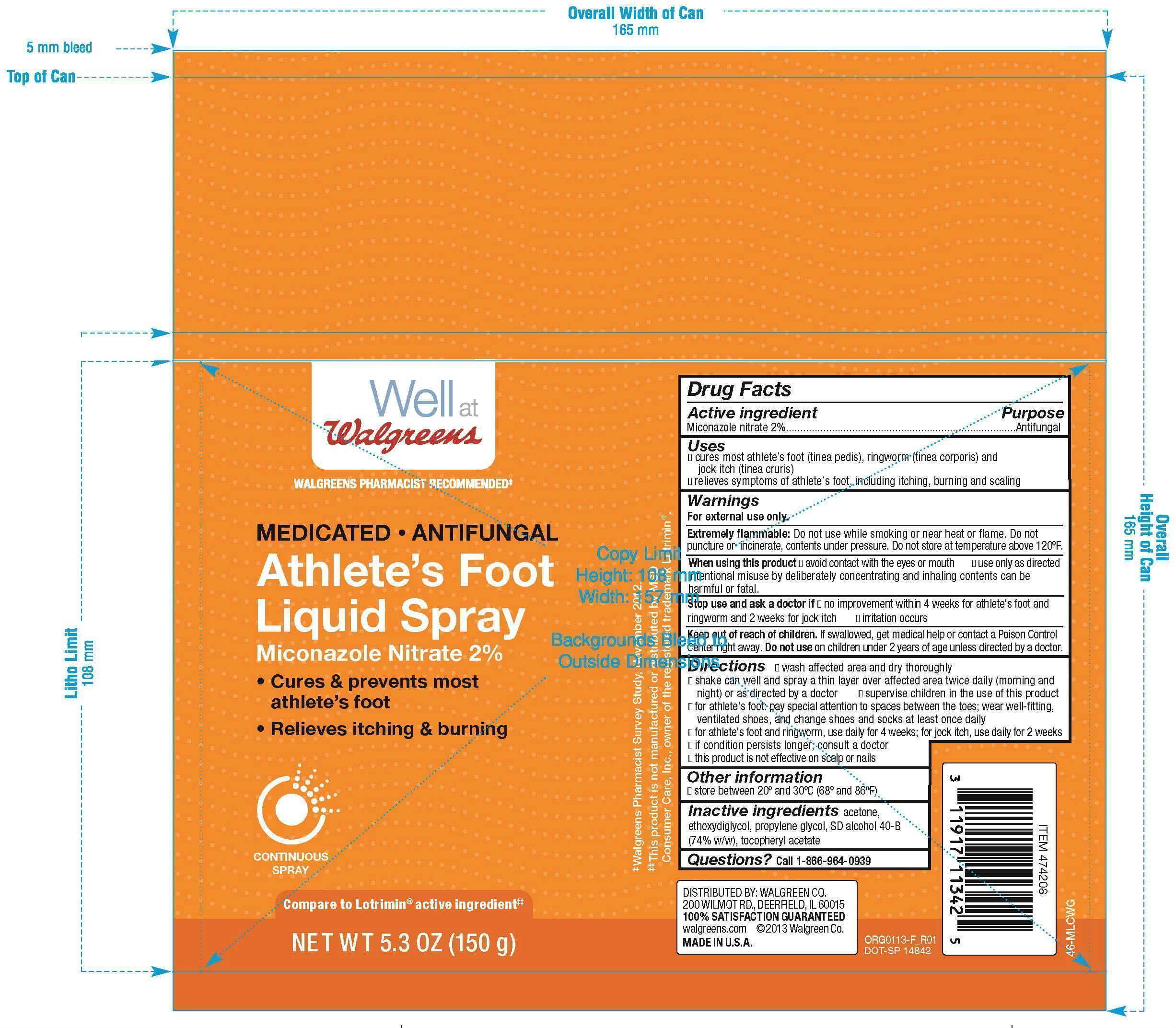 DRUG LABEL: Miconazole Nitrate
NDC: 0363-4208 | Form: SPRAY
Manufacturer: Walgreens Company
Category: otc | Type: HUMAN OTC DRUG LABEL
Date: 20251106

ACTIVE INGREDIENTS: MICONAZOLE NITRATE 3 g/150 g
INACTIVE INGREDIENTS: ACETONE; DIETHYLENE GLYCOL MONOETHYL ETHER; PROPYLENE GLYCOL; ALCOHOL; .ALPHA.-TOCOPHEROL ACETATE

Walgreens Miconazole Athlete's Foot Liquid Spray

Active ingredient

Miconazole nitrate 2%

Purpose

Antifungal

Uses

- cures most athlete's foot (linea pedis), ringworm (linea corporis) and jock itch (linea cruris)
- relieves symptoms of athlete's foot, including itching burning and cracking

Warnings

For external use only.

Extremely flammable:

Do not use while smoking or near heat or flame. Do not puncture or incinerate, contents under pressure. Do not store at temperature above 120ºF.

When using this product

- avoid contact with the eyes or mouth
- use only as directed

Intentional misuse by deliberately concentrating and inhaling contents cans be harmful or fatal.

Stop use and ask a doctor if

- no improvement within 4 weeks for athlete's foot and ringworm; 2 weeks for jock itch
- irritation occurs

Keep out of reach of children.

If swallowed, get medical help or contact a Poison Control Center right away. Do not use on children under 2 years of age unless directed by a doctor.

Directions

- wash affected area and dry thoroughly
- shake can well and spray a thin layer over affected area twice daily (morning and night) or as directed by a doctor
- supervise children in the use of this product
- for athlete's foot: pay special attention to spaces between the toes; wear well-fitting, ventilated shoes, and change shoes and socks at least once daily
- for athlete's foot and ringworm, use daily for 4 weeks; for jock itch, use daily for 2 weeks
- if conditions persist, consult a doctor
- this product is not effective on the scalp or nails

Other information

store between 20º and 30ºC (68ºF and 86º)

Inactive ingredients

acetone, ethoxyglycol, propylene glycol, SD alcohol 40-B (74%w/w), tocopheryl acetate

Questions?

call 1-866-964-0939

Principal Display Panel

Well at Walgreens

Medicated • Antifungal

Athlete's Foot Liquid Spray

Miconazole Nitrate 2%

- Cures & prevents most athlete's foot
- Relieves itching and burning

NET WT 5.3 OZ (150g)